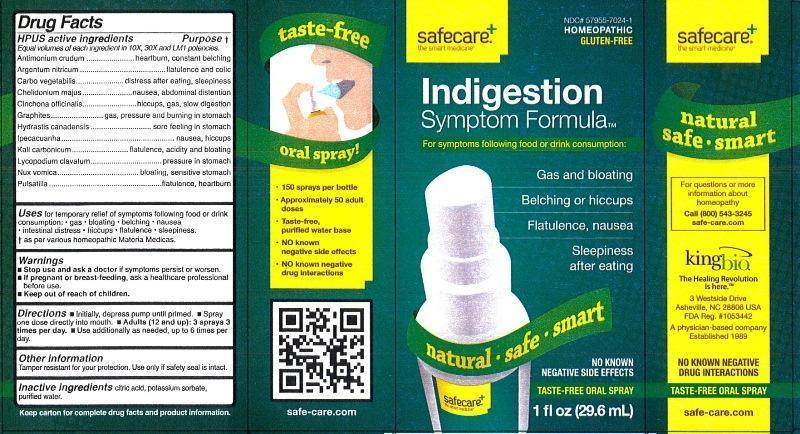 DRUG LABEL: Indigestion Symptom Formula
NDC: 57955-7024 | Form: LIQUID
Manufacturer: King Bio Inc.
Category: homeopathic | Type: HUMAN OTC DRUG LABEL
Date: 20130220

ACTIVE INGREDIENTS: ANTIMONY TRISULFIDE 10 [hp_X]/29.6 mL; SILVER NITRATE 10 [hp_X]/29.6 mL; ACTIVATED CHARCOAL 10 [hp_X]/29.6 mL; CHELIDONIUM MAJUS 10 [hp_X]/29.6 mL; CINCHONA OFFICINALIS BARK 10 [hp_X]/29.6 mL; GRAPHITE 10 [hp_X]/29.6 mL; GOLDENSEAL 10 [hp_X]/29.6 mL; IPECAC 10 [hp_X]/29.6 mL; POTASSIUM CARBONATE 10 [hp_X]/29.6 mL; LYCOPODIUM CLAVATUM SPORE 10 [hp_X]/29.6 mL; STRYCHNOS NUX-VOMICA SEED 10 [hp_X]/29.6 mL; PULSATILLA VULGARIS 10 [hp_X]/29.6 mL
INACTIVE INGREDIENTS: CITRIC ACID MONOHYDRATE; POTASSIUM SORBATE; WATER

Indigestion Symptom Formula

Active Ingredients

HPUS active ingredients

Equal volumes of each ingredient in 10X, 30X and LM1 potencies.

Antimonium crudum, Argentum nitricum, Carbo vegetabilis, Chelidonium majus, Cinchona officinalis, Graphites, Hydrastis canadensis, Ipecacuanha, Kali carbonicum, Lycopodium clavatum, Nux vomica, Pulsatilla

INACTIVE INGREDIENT

Inactive ingredients:Citric acid, potassium sorbate and purified water.

Purpose

HPUS active ingredients Purpose†

Equal volumes of each ingredient in 10X, 30X and LM1 potencies.

Antimonium crudum..................................................heartburn, constant belching

Argentum nitricum....................................................flatulence and colic

Carbo vegetabilis.....................................................distress after eating, sleepiness

Chelidonium majus...................................................nausea, abdominal distention

Cinchona officinalis...................................................hiccups, gas, slow digestion

Graphites.................................................................gas, pressure and burning in stomach

Hydrastis canadensis...............................................sore feeeling in stomach

Ipecacuanha............................................................nausea, hiccups

Kali carbonicum........................................................flatulence, acidity and bloating

Lycopodium clavatum...............................................pressure in stomach

Nux vomica...............................................................bloating, sensitive stomach

Pulsatilla...................................................................flatulence, heartburn

Indication and Usage

Uses for temporary relief of symptoms following food or drink consumption:

- gas
- bloating
- belching
- nausea
- intestinal distress
- hiccups
- flatulence
- sleepiness

† as per various homeopathic Materia Medicas.

Warnings

- Stop use and ask a doctor if symptoms persist or worsen.
- If pregnant or breast-feeding, ask a healthcare professional before use.
- Keep out of reach of children.

Other information: Tamper resistant for your protection. Use only if safety seal is intact.

Keep out of reach of children

Dosage and Administration

Directions

- Initially, depress pump until primed.
- Spray one dose directly into mouth
- Adults (12 and up): 3 sprays 3 times per day.
- Use additionally as needed, up to 6 times per day.

PACKAGE LABEL

King Bio Inc.

3 Westside Drive

Asheville, NC 28806

For questions or more information about homeopathy

Call (800) 543-3245 or safe-care.com